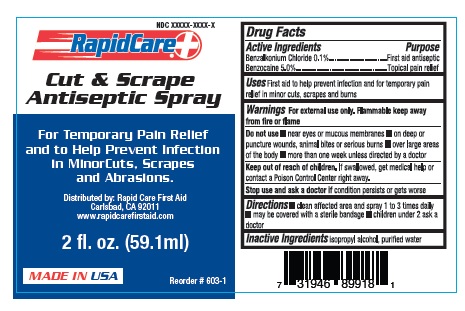 DRUG LABEL: Antiseptic
NDC: 73659-011 | Form: SPRAY
Manufacturer: Rapid Care, Inc
Category: otc | Type: HUMAN OTC DRUG LABEL
Date: 20211014

ACTIVE INGREDIENTS: BENZALKONIUM CHLORIDE 0.001 mg/1 1; BENZOCAINE 0.05 mg/1 1
INACTIVE INGREDIENTS: ISOPROPYL ALCOHOL; WATER

RapidCare - Antiseptic Spray- 2fl oz

Active Ingredients

Benzalkonium Chloride 0.1%

Benzocaine 5.0%

Purpose

First aid antiseptic

Topical pain relief

Uses

First aid to help prevent infection and for temporary pain relief in minor cuts and burns

Warnings

For external use only. Flammable keep away from fire or flame.

Do Not Use

- near eyes or mucous membranes
- on deep or puncture wounds, animal bites or serious burns
- over lare areas of the body
- more than one week unless directed by a doctor

Keep out of reach of children.

If swallowed get medical help or contact a Poison Control right away.

Stop use and ask a doctor

if condition persists or gets worse

Directions

- clean the affected area and spray 1 to 3 times daily
- may be covered with a sterile bandage
- childern under 2 ask a doctor

Inactive ingredient

Isopropyl alcohol, purified water